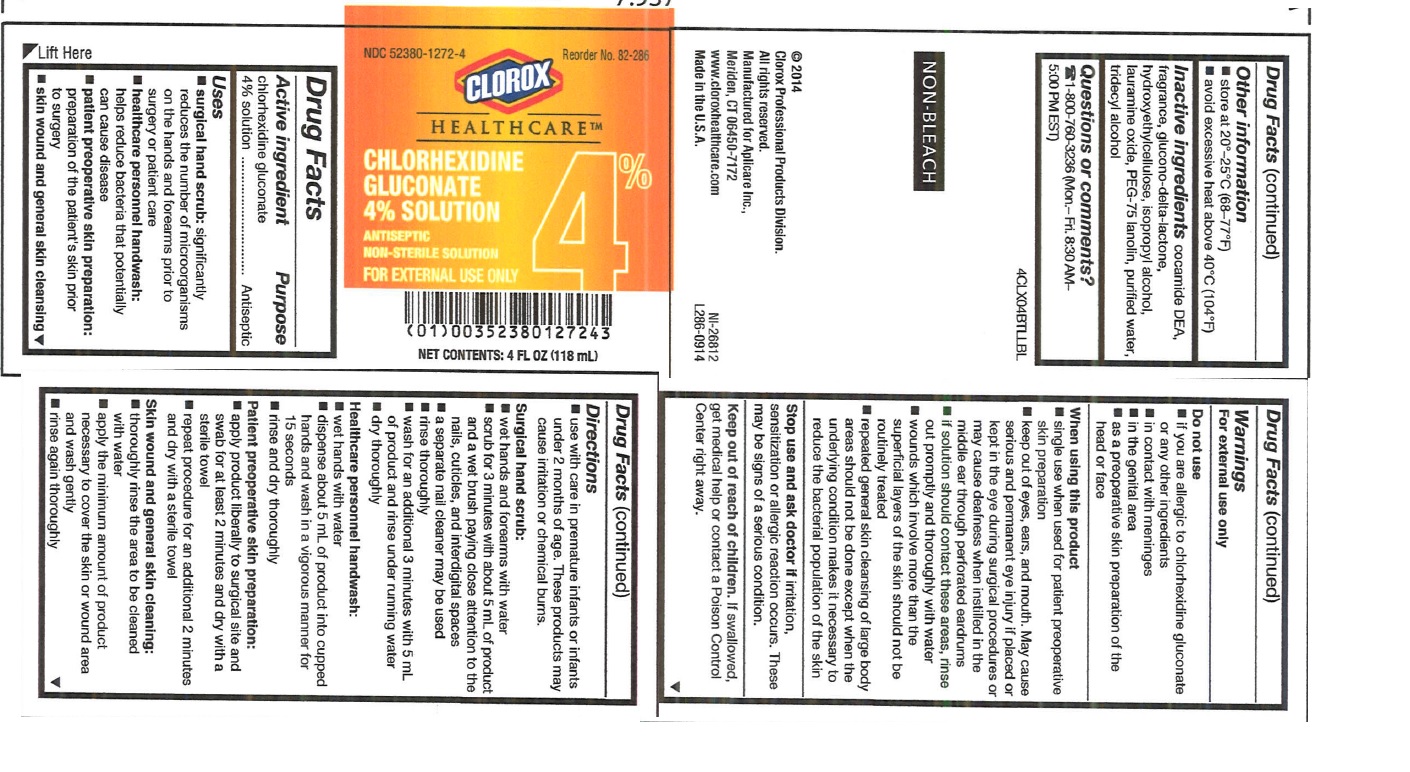 DRUG LABEL: Aplicare Antiseptic Chlorhexidine Gluconate
NDC: 52380-1272 | Form: SOLUTION
Manufacturer: Aplicare, Inc.
Category: otc | Type: HUMAN OTC DRUG LABEL
Date: 20150811

ACTIVE INGREDIENTS: CHLORHEXIDINE GLUCONATE 4 g/100 mL
INACTIVE INGREDIENTS: COCO DIETHANOLAMIDE; GLUCONOLACTONE; HYDROXYETHYL CELLULOSE (140 CPS AT 5%); ISOPROPYL ALCOHOL; LAURAMINE OXIDE; WATER

Drug Facts

Active ingredient

Chlorhexidine Gluconate 4% solution

Purpose

Antiseptic

Uses

- surgical hand scrub: significantly reduces the number of microorganisms on the hands and forearms prior to surgery or patient care
- healthcare personnel handwash: helps reduce bacteria that potentially can cause disease
- patient preoperative skin preparation: for the preparation of the patient's skin prior to surgery
- skin wound and general skin cleansing

Warnings

For external use only

Do not use

- if you are allergic to chlorhexidine gluconate or any other ingredients
- in contact with meninges
- in the genital area
- as a preoperative skin prep of the head or face

When using this product

- single use when used for patient preoperative skin preparation
- keep out of eyes, ears and mouth. May cause serious and permanent eye injury if placed or kept in the eye during surgical procedures or may cause deafness when installed in the middle ear through perforated ear drums.
- if solution should contact these areas, rinse out promptly and thoroughly with water
- wounds which involve more than the superficial layers of the skin should not be routinely treated
- repeated general skin cleansing of large body areas should not be done except when the underlying condition makes it necessary to reduce the bacterial population of the skin

Stop use and ask a doctor if irritation, sensitization or allergic reaction occurs. This may be signs of a serious condition.

Keep out of reach of children.

If swallowed, get medical help or contact a Poison Control Center right away.

Directions

- use with care on premature infants or infants under 2 months of age. These products may cause irritation or chemical burns

Surgical hand scrub:

- wet hands and forearms with water
- scrub for 3 minutes with about 5 mL of product with and a wet brush, paying close attention to the nails, cuticles and interdigital spaces
- a separate nail cleaner may be used
- rinse thoroughly
- wash for an additional 3 minutes with 5 mL of product and rinse under running water
- dry thoroughly

Healthcare personnel handwash:

- wet hands with water
- dispense about 5 ml of product into cupped hands and wash in a vigorous manner for 15 seconds
- rinse and dry thoroughly

Patient preoperative skin preparation:

- apply product liberally to surgical site and swab for at least 2 minutes and dry with a sterile towel
- repeat procedure for an additional 2 minutes and dry with a sterile towel

Skin wound and general skin cleansing:

- thoroughly rinse the area to be cleaned with water
- apply the minimum amount of product necessary to cover the skin or wound area and wash gently
- rinse again thoroughly

Inactive ingredients

cocamide DEA, fragrance, glucono-delta-lactone, hydroxyethylcellulose, isopropyl alcohol, lauramine oxide, PEG-75 lanolin, purified water, tridecyl alcohol

Questions or comments?

1-800-760-3236 (Mon.-Fri. 8:30AM - 5:00 PM EST)

PACKAGE LABEL

4% Chlorhexidine Gluconate